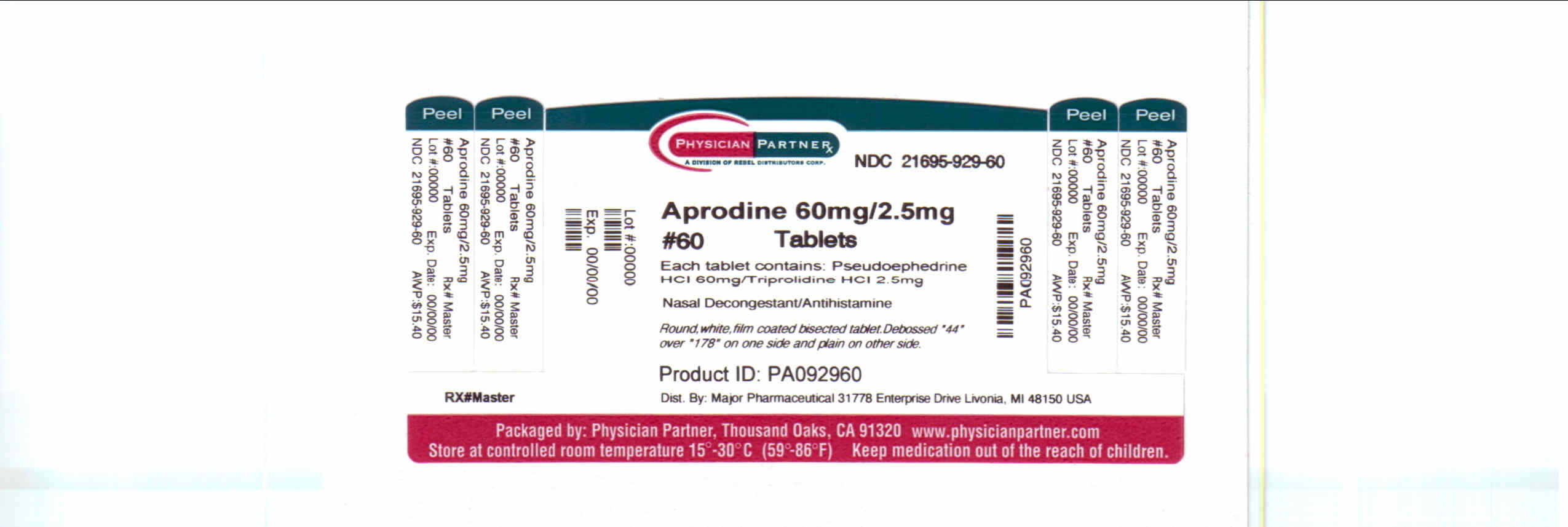 DRUG LABEL: Aprodine
NDC: 21695-929 | Form: TABLET, FILM COATED
Manufacturer: Rebel Distributors Corp
Category: otc | Type: HUMAN OTC DRUG LABEL
Date: 20110810

ACTIVE INGREDIENTS: PSEUDOEPHEDRINE HYDROCHLORIDE 60 mg/1 1; TRIPROLIDINE HYDROCHLORIDE 2.5 mg/1 1
INACTIVE INGREDIENTS: HYPROMELLOSES; LACTOSE; MAGNESIUM STEARATE; CELLULOSE, MICROCRYSTALLINE; POLYETHYLENE GLYCOL; STEARIC ACID; TITANIUM DIOXIDE

Aprodine

Active ingredient(s)

Pseudoephedrine HCl 60 mg

Triprolidine HCl 2.5 mg

Purpose

Nasal decongestant

Antihistamine

Use(s)

temporarily relieves these symptoms due to hay fever or other upper respiratory allergies:
runny nose
itchy, watery eyes
sneezing
itching of the nose or throat
temporarily relieves nasal congestion due to the common cold

Warnings

Do not use

if you are now taking a prescription monoamine oxidase inhibitor (MAOI) (certain drugs for depression, psychiatric or emotional conditions, or Parkinson’s disease), or for 2 weeks after stopping the MAOI rug. If you do not know if your prescription drug contains an MAOI, ask a doctor or pharmacist before taking this product.

Ask a doctor before use if you have

high blood pressure
heart disease
thyroid disease
diabetes
glaucoma
a breathing problem such as emphysema or chronic bronchitis
trouble urinating due to an enlarged prostate gland

Ask a doctor or pharmacist before use if you are

taking sedatives or tranquilizers

When using this product

do not exceed recommended dose
excitability may occur, especially in children
drowsiness may occur
avoid alcoholic drinks
alcohol, sedatives and tranquilizers may increase drowsiness
be careful when driving a motor vehicle or operating machinery

Stop use and ask a doctor if

nervousness, dizziness or sleeplessness occur
symptoms do not improve within 7 days or occur with a fever

If pregnant or breast-feeding,

ask a health professional before use.

Keep out of reach of children

In case of overdose, get medical help or contact a Poison Control Center right away.

Directions

adults and children 12 years and over: take 1 tablet every 4 to 6 hours. Do not take more than 4 tablets in 24 hours.
children under 12 years: do not use this product in children under 12 years of age

Other information

store at controlled room temperature 15°-30°C (59°-86°F)
see end flap for expiration date and lot number

Inactive ingredients

corn starch, hypromellose, lactose, magnesium stearate, microcrystalline cellulose, polyethylene glycol, silica gel, stearic acid, titanium dioxide

Questions or comments?

To Report Adverse Drug Event Call: (800) 616-2471